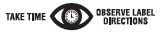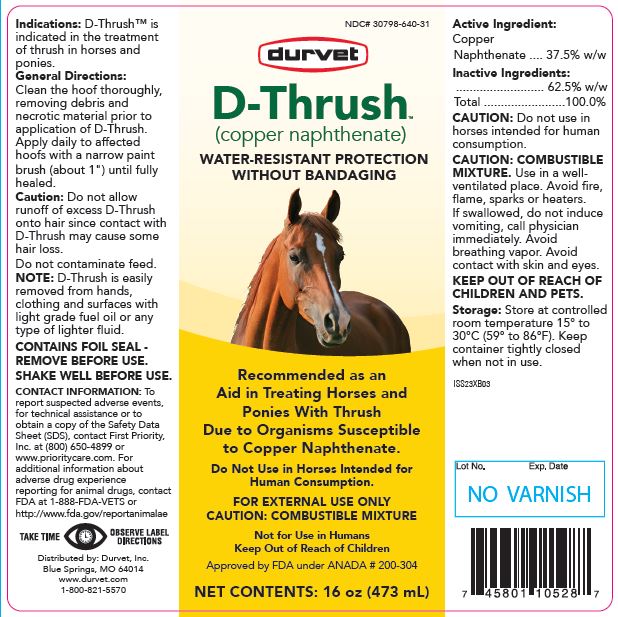 DRUG LABEL: D-THRUSH
NDC: 30798-640 | Form: LIQUID
Manufacturer: DURVET INCORPORATED
Category: animal | Type: OTC ANIMAL DRUG LABEL
Date: 20231005

ACTIVE INGREDIENTS: COPPER NAPHTHENATE 0.825 g/1 mL

D-THRUSH™

VETERINARY INDICATIONS

(copper naphthenate)

Water-Resistant Protection

Recommended as an Aid in Treating Horses and Ponies With Thrush Due to Organisms Susceptible to Copper Naphthenate.
Do Not Use in Horses Intended for Human Consumption.
FOR EXTERNAL USE ONLY
CAUTION: COMBUSTIBLE MIXTURE
Not for Use in Humans
Keep Out of Reach of Children
Approved by FDA under ANADA # 200-304

NET CONTENTS:

16 oz (473 mL)

Indications:

D-Thrush™ is indicated in the treatment of thrush in horses and ponies.

General Directions:

Clean the hoof thoroughly, removing debris and necrotic material prior to application of D-Thrush™. Apply daily to affected hoofs with a narrow paint brush (about 1") until fully healed.

Caution:

Do not allow runoff of excess D-Thrush onto hair since contact with D-Thrush may cause some hair loss.
Do not contaminate feed.

NOTE:

D-Thrush™ is easily removed from hands, clothing and surfaces with light grade fuel oil or any type of lighter fluid.

CONTAINS FOIL SEAL – REMOVE BEFORE USE.

SHAKE WELL BEFORE USE.

CONTACT INFORMATION:

To report suspected adverse events, for technical assistance or to obtain a copy of the Safety Data Sheet (SDS), contact First Priority, Inc. at (800) 650-4899 or www.prioritycare.com. For additional information about adverse drug experience reporting for animal drugs, contact FDA at 1-888-FDA-VETS or http://www.fda.gov/reportanimalae

Active Ingredient:

Copper Naphthenate ..........37.5% w/w

Inactive Ingredients:

..........................62.5% w/w

Total .......................100.0%

CAUTION:

Do not use in horses intended for human consumption.

CAUTION: COMBUSTIBLE MIXTURE. Use in a well-ventilated place. Avoid fire, flame, sparks or heaters.

If swallowed, do not induce vomiting, call physician immediately. Avoid breathing vapor. Avoid contact with skin and eyes.

KEEP OUT OF REACH OF CHILDREN AND PETS.

STORAGE:

Store at controlled room temperature 15° to 30°C (59° to 86°F). Keep container tightly closed when not in use.

INFORMATION FOR OWNERS/CAREGIVERS

Distributed by: Durvet, Inc.
Blue Springs, MO 64014
www.durvet.com
1-800-821-5570

Rev. ISS23XB03